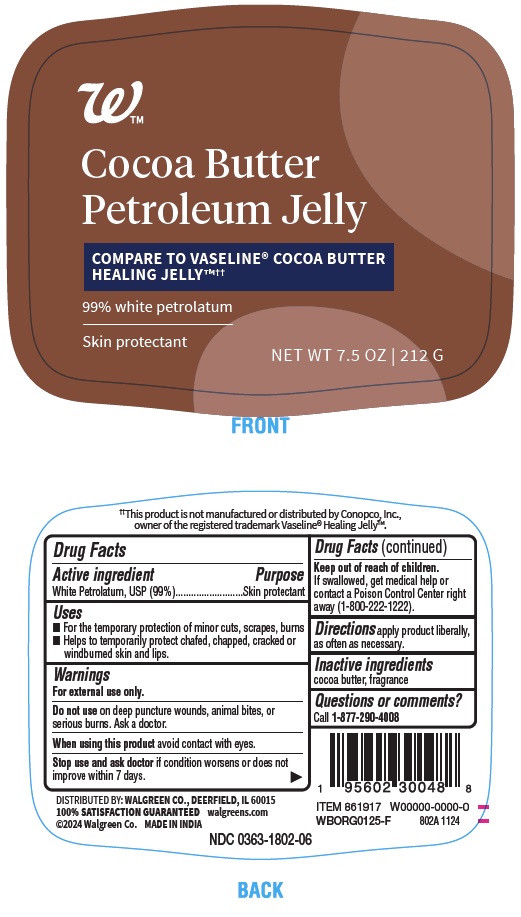 DRUG LABEL: Cocoa Butter Petroleum Jelly
NDC: 0363-1802 | Form: JELLY
Manufacturer: WALGREENS
Category: otc | Type: HUMAN OTC DRUG LABEL
Date: 20250326

ACTIVE INGREDIENTS: WHITE PETROLATUM 99 g/100 g
INACTIVE INGREDIENTS: COCOA BUTTER

802A Walgreens Petroleum Jelly

Active ingredient
White Petrolatum, USP (99%)

Purpose
Skin protectant

Uses

- For the temporary protection of minor cuts, scrapes, burns
- Helps to temporarily protect chafed, chapped, cracked or windburned skin and lips.

Warnings
For external use only.

Do not use on deep puncture wounds, animal bites, or serious burns. Ask a doctor.

When using this product avoid contact with eyes.

Stop use and ask doctor if condition worsens or does not improve within 7 days.

Keep out of reach of children. If swallowed, get medical help or contact a Poison Control Center right away (1-800-222-1222).

DOSAGE AND ADMINISTRATION

Directions apply product liberally, as often as necessary.

Inactive ingredients cocoa butter, fragrance

Questions or comments? Call 1-877-290-4008